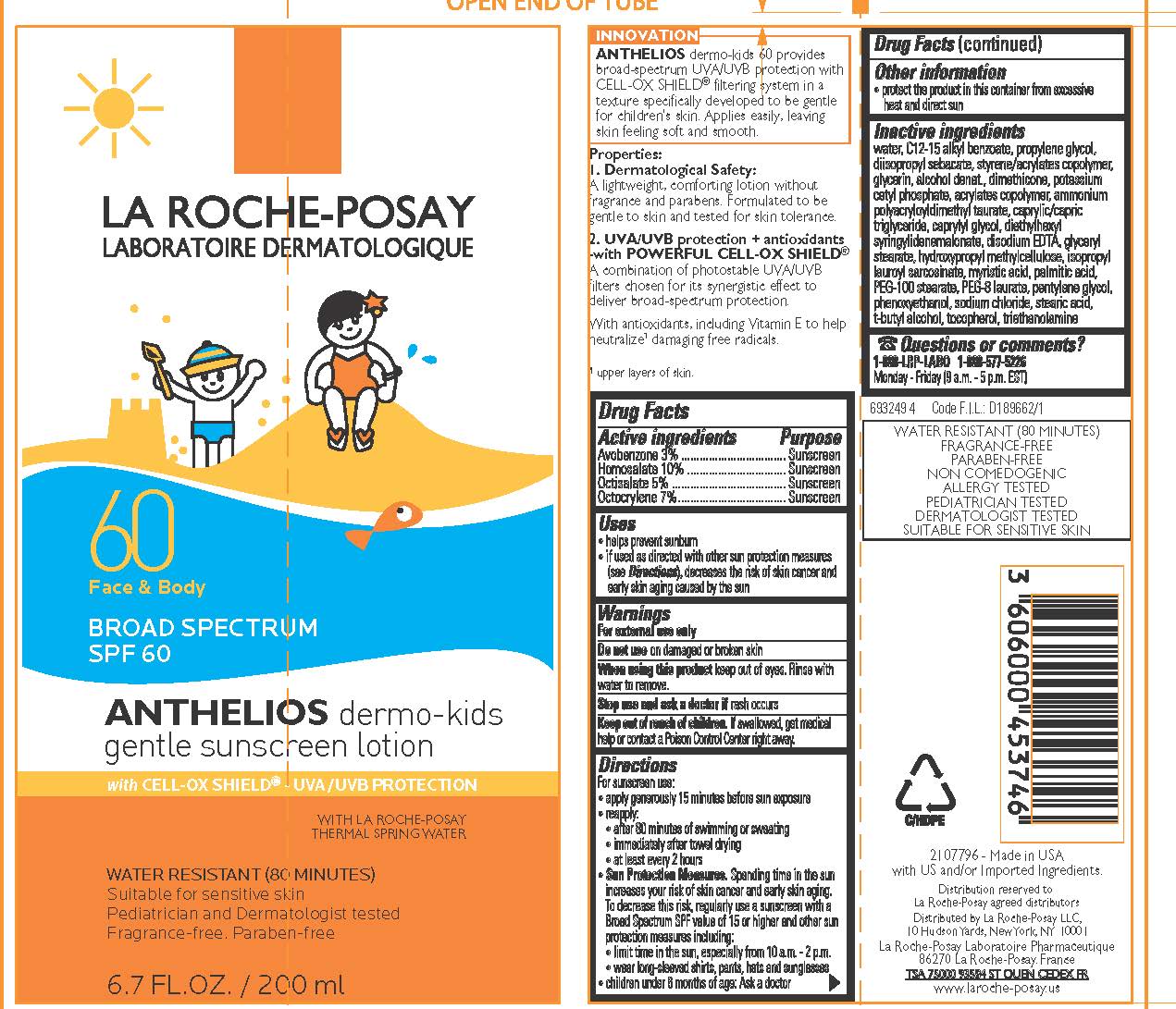 DRUG LABEL: La Roche Posay Laboratoire Dermatologique Anthelios Dermo Kids Gentle Face and Body Broad Spectrum SPF 60 Sunscreen Water Resistant 80 Minutes
NDC: 49967-374 | Form: LOTION
Manufacturer: L'Oreal USA Products Inc
Category: otc | Type: HUMAN OTC DRUG LABEL
Date: 20231231

ACTIVE INGREDIENTS: AVOBENZONE 30 mg/1 mL; HOMOSALATE 100 mg/1 mL; OCTISALATE 50 mg/1 mL; OCTOCRYLENE 70 mg/1 mL
INACTIVE INGREDIENTS: WATER; ALKYL (C12-15) BENZOATE; PROPYLENE GLYCOL; DIISOPROPYL SEBACATE; GLYCERIN; ALCOHOL; DIMETHICONE; POTASSIUM CETYL PHOSPHATE; BUTYL ACRYLATE/METHYL METHACRYLATE/METHACRYLIC ACID COPOLYMER (18000 MW); AMMONIUM POLYACRYLOYLDIMETHYL TAURATE (55000 MPA.S); MEDIUM-CHAIN TRIGLYCERIDES; CAPRYLYL GLYCOL; DIETHYLHEXYL SYRINGYLIDENEMALONATE; EDETATE DISODIUM; GLYCERYL MONOSTEARATE; HYPROMELLOSE, UNSPECIFIED; ISOPROPYL LAUROYL SARCOSINATE; MYRISTIC ACID; PALMITIC ACID; PEG-100 STEARATE; PEG-8 LAURATE; PENTYLENE GLYCOL; PHENOXYETHANOL; SODIUM CHLORIDE; STEARIC ACID; TERT-BUTYL ALCOHOL; TOCOPHEROL; TROLAMINE

Drug Facts

Active ingredient

Avobenzone 3%

Homosalate 10%

Octisalate 5%

Octocrylene 7%

Purpose

Sunscreen

Uses

- helps prevent sunburn
- if used as directed with other sun protection measures (see Directions), decreases the risk of skin cancer and early skin aging caused by the sun

Warnings

For external use only

Do not use

on damaged or broken skin

When using this product

keep out of eyes. Rinse with water to remove.

Stop use and ask a doctor if

rash occurs

Keep out of reach of children.

If swallowed, get medical help or contact a Poison Control Center right away.

Directions

For sunscreen use:

● apply generously 15 minutes before sun exposure

● reapply:

● after 80 minutes of swimming or sweating

● immediately after towel drying

● at least every 2 hours

● Sun Protection Measures. Spending time in the sun increases your risk of skin cancer and early skin aging. To decrease this risk, regularly use a sunscreen with a Broad Spectrum SPF value of 15 or higher and other sun protection measures including:

● limit time in the sun, especially from 10 a.m. – 2 p.m.

● wear long-sleeved shirts, pants, hats, and sunglasses

● children under 6 months of age: Ask a doctor

Other information

protect the product in this container from excessive heat and direct sun

Inactive ingredients

water, C12-15 alkyl benzoate, propylene glycol, diisopropyl sebacate, styrene/acrylates copolymer, glycerin, alcohol denat., dimethicone, potassium cetyl phosphate, acrylates copolymer, ammonium polyacryloyldimethyl taurate, caprylic/capric triglyceride, caprylyl glycol, diethylhexyl syringylidenemalonate, disodium EDTA, glyceryl stearate, hydroxypropyl methylcellulose, isopropyl lauroyl sarcosinate, myristic acid, palmitic acid, PEG-100 stearate, PEG-8 laurate, pentylene glycol, phenoxyethanol, sodium chloride, stearic acid, t-butyl alcohol, tocopherol, triethanolamine

Questions or comments?

1-888-LRP-LABO 1-888-577-5226

Monday - Friday (9 a.m. - 5 p.m. EST)